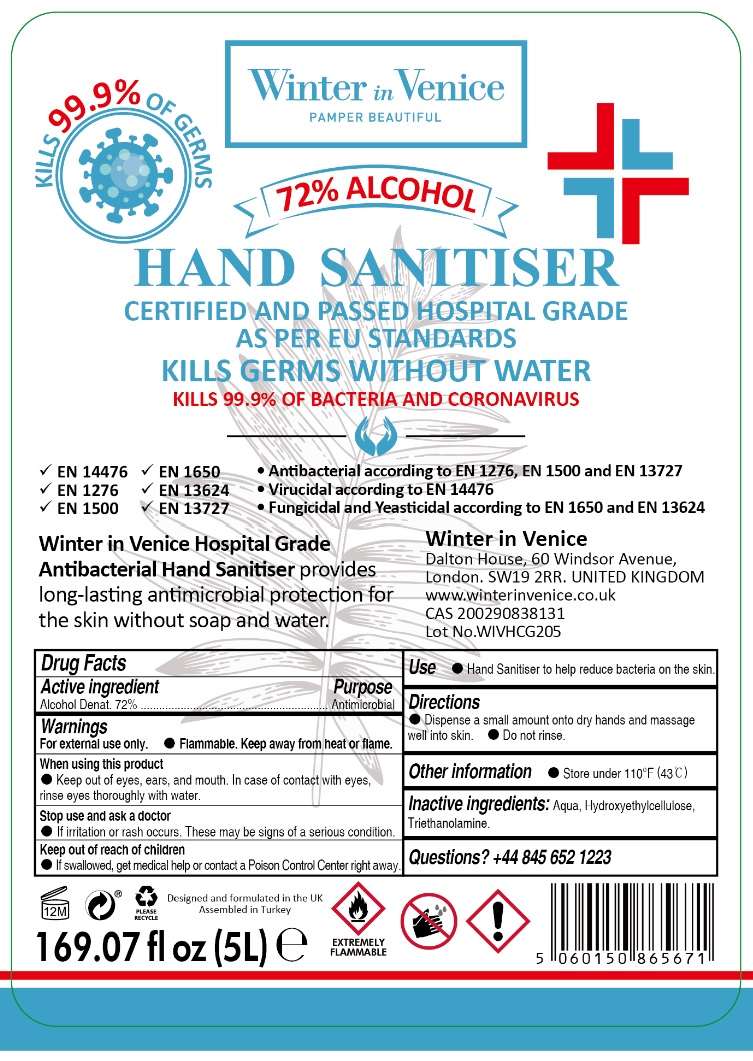 DRUG LABEL: Winter in Venice HOSPITAL GRADE HAND SANITIZER
NDC: 78609-125 | Form: GEL
Manufacturer: WIV GLOBAL LIMITED
Category: otc | Type: HUMAN OTC DRUG LABEL
Date: 20201005

ACTIVE INGREDIENTS: ALCOHOL 72 L/100 L
INACTIVE INGREDIENTS: WATER; HYDROXYETHYL CELLULOSE, UNSPECIFIED; TROLAMINE

Winter in Venice HOSPITAL GRADE HAND SANITIZER

Active ingredient

Alcohol Denat. 72%

Purpose

Antimicrobial

Warnings

For external use only. • Flammable. Keep away from heat or flame.

When using this product
• Keep out of eyes, ears, and mouth. In case of contact with eyes, rinse eyes thoroughly with water.

Stop use and ask a doctor
• if irritation or rash occurs. These may be signs of a serious condition.

Keep out of reach of children

• If swallowed, get medical help or contact a Poison Control Center right away.

INDICATIONS AND USAGE

Use • Hand Sanitiser to help reduce bacteria on the skin.

Directions

• Dispense a small amount onto dry hands and massage well into skin. • Do not rinse.

Other information • Store under 110°F (43°C)

Inactive ingredients : Aqua, Hydroxyethylcellulose, Triethanolamine.

Questions? +44 845 652 1223

KILLS 99.9% OF GERMS

72% ALCOHOL
CERTIFIED AND PASSED HOSPITAL GRADE AS PER EU STANDARDS
KILLS GERMS WITHOUT WATER
KILLS 99.9% OF BACTERIA AND CORONAVIRUS

• EN 14476
• EN 1276
• EN 1500
• EN 1650
• EN 13624
• EN 13727

• Antibacterial according to EN 1276, EN 1500 and EN 13727
• Virucidal according to EN 14476
• Fungicidal and Yeasticidal according to EN 1650 and EN 13624

Winter in Venice Hospital Grade Antibacterial Hand Sanitiser provides long-lasting antimicrobial protection for the skin without soap and water

Winter in Venice
Dalton House, 60 Windsor Avenue,
London. SW19 2RR. UNITED KINGDOM
www.winterinvenice.co.uk

Designed and formulated in the UK
Assembled in Turkey

EXTREMELY FLAMMABLE